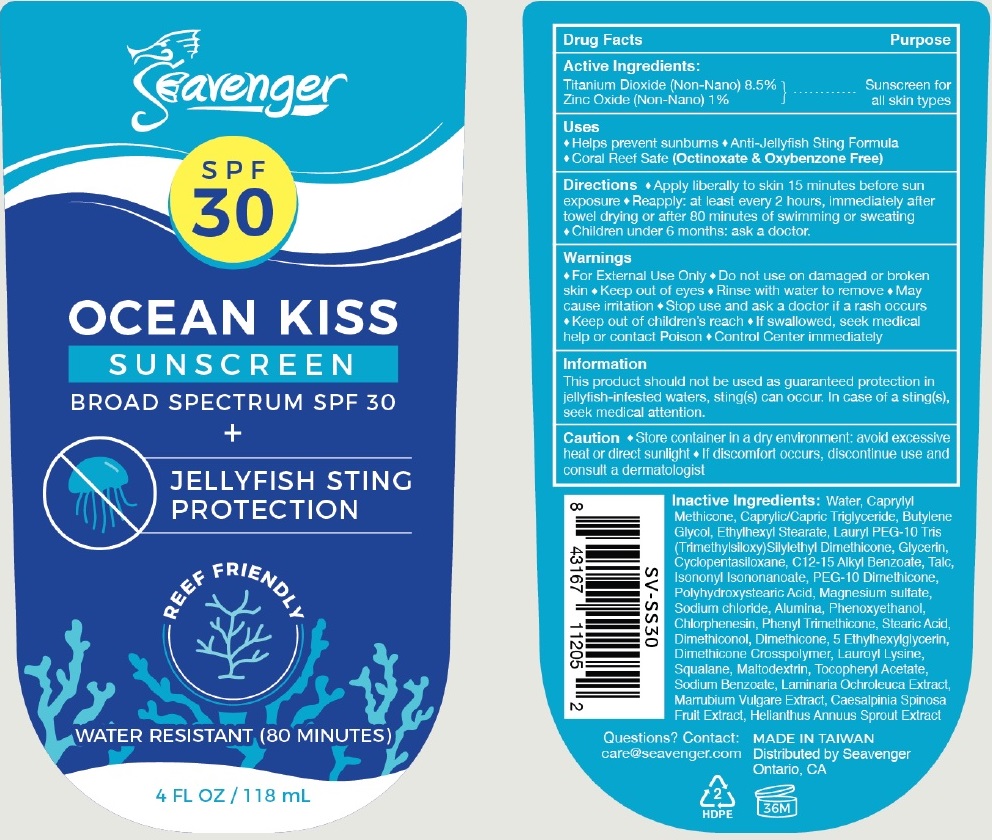 DRUG LABEL: Seavenger ocean kiss sunscreen SPF 30
NDC: 82588-000 | Form: CREAM
Manufacturer: SHOP 709 Corp
Category: otc | Type: HUMAN OTC DRUG LABEL
Date: 20231226

ACTIVE INGREDIENTS: TITANIUM DIOXIDE 85 mg/1 mL; ZINC OXIDE 10 mg/1 mL
INACTIVE INGREDIENTS: LAUROYL LYSINE; SQUALANE; MALTODEXTRIN; .ALPHA.-TOCOPHEROL ACETATE; SODIUM BENZOATE; LAMINARIA OCHROLEUCA; HELIANTHUS ANNUUS SPROUT; WATER; CAPRYLYL TRISILOXANE; MEDIUM-CHAIN TRIGLYCERIDES; BUTYLENE GLYCOL; ETHYLHEXYL STEARATE; GLYCERIN; CYCLOMETHICONE 5; ALKYL (C12-15) BENZOATE; TALC; ISONONYL ISONONANOATE; MAGNESIUM SULFATE, UNSPECIFIED FORM; SODIUM CHLORIDE; ALUMINUM OXIDE; PHENOXYETHANOL; CHLORPHENESIN; PHENYL TRIMETHICONE; STEARIC ACID; DIMETHICONE; ETHYLHEXYLGLYCERIN

Seavenger ocean kiss sunscreen SPF 30

Active Ingredients:

Titanium Dioxide (Non-Nano) 8.5%
Zinc Oxide (Non-Nano) 1%

Purpose

Sunscreen for all skin types

Uses

- Helps prevent sunburns
- Anti-Jellyfish Sting Formula
- Coral Reef Safe (Octinoxate & Oxybenzone Free)

Directions

- Apply liberally to skin 15 minutes before sun exposure
- Reapply: at least every 2 hours, immediately after towel drying or after 80 minutes of swimming or sweating
- Children under 6 months: ask a doctor.

Warnings

- For External Use Only

Do not use

- on damaged or broken skin
- Keep out of eyes
- Rinse with water to remove
- May cause irritation

Stop use and ask a doctor

- if a rash occurs

Keep out of children's reach

- If swallowed, seek medical help or contact Poison
- Control Center immediately

Information

This product should not be used as guarateed protection in jellyfish-infested waters, sting(s) can occur. In case of a sting(s), seek medical attention.

Caution

- Store container in a dry environment:avoid excessive heat or direct sunlight
- If discomfort occurs, discontinue use and consult a dermatologist

Inactive Ingredients:

Water, Caprylyl Methicone, Caprylic/Capric Triglyceride, Butylene Glycol, Ethylhexyl Stearate, Lauryl PEG-10 Tris (Trimethylsiloxy) Silylethyl Dimethicone, Glycerin, Cyclopentasiloxane, C12-15 Alkyl Benzoate, Talc, Isononyl Isononanoate, PEG-10 Dimethicone, Polyhydroxystearic Acid, Magnesium sulfate, Sodium chloride, Alumina, Phenoxyethanol, Chlorphenesin, Phenyl Trimethicone, Stearic Acid, Dimethiconol, Dimethicone, 5 Ethylhexylglycerin, Dimethiconol Crosspolymer, Lauroyl Lysine, Squalane, Maltodextrin, Tocopheryl Acetate, Maltodextrin, Tocopheryl Acetate, Sodium Benzoate, Laminaria Ochroleuca Extract, Marrubium Vulare Extract, Caesalpinia Spinosa Fruit Extract, Helianthus Annuus Sprout Extract

Questions?

Contact: care@seavenger.com